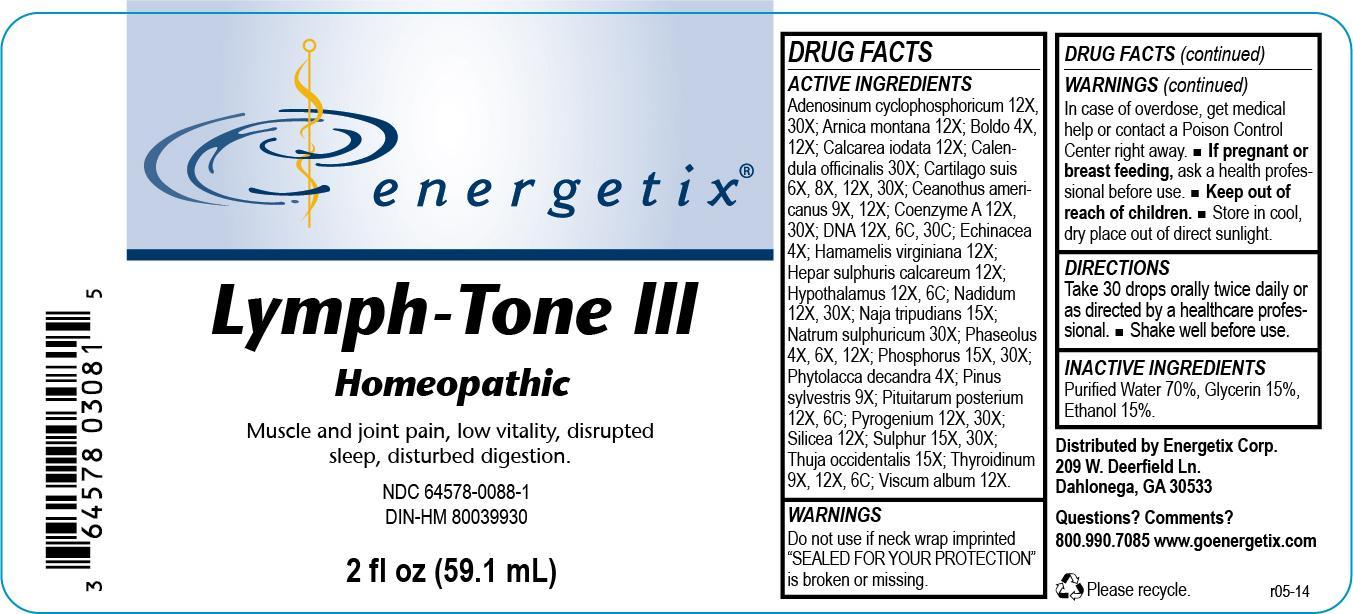 DRUG LABEL: Lymph-Tone III
NDC: 64578-0088 | Form: LIQUID
Manufacturer: Energetix Corp
Category: homeopathic | Type: HUMAN OTC DRUG LABEL
Date: 20140206

ACTIVE INGREDIENTS: ADENOSINE CYCLIC PHOSPHATE 12 [hp_X]/59.1 mL; ARNICA MONTANA 12 [hp_X]/59.1 mL; PEUMUS BOLDUS LEAF 3 [hp_X]/59.1 mL; CALCIUM IODIDE 12 [hp_X]/59.1 mL; CALENDULA OFFICINALIS FLOWERING TOP 30 [hp_X]/59.1 mL; SUS SCROFA CARTILAGE 6 [hp_X]/59.1 mL; CEANOTHUS AMERICANUS LEAF 9 [hp_X]/59.1 mL; COENZYME A 12 [hp_X]/59.1 mL; HERRING SPERM DNA 12 [hp_X]/59.1 mL; ECHINACEA ANGUSTIFOLIA 4 [hp_X]/59.1 mL; HAMAMELIS VIRGINIANA ROOT BARK/STEM BARK 12 [hp_X]/59.1 mL; CALCIUM SULFIDE 12 [hp_X]/59.1 mL; BOS TAURUS HYPOTHALAMUS 12 [hp_X]/59.1 mL; NADIDE 12 [hp_X]/59.1 mL; NAJA NAJA VENOM 15 [hp_X]/59.1 mL; SODIUM SULFATE 30 [hp_X]/59.1 mL; KIDNEY BEAN 4 [hp_X]/59.1 mL; PHOSPHORUS 15 [hp_X]/59.1 mL; PHYTOLACCA AMERICANA ROOT 4 [hp_X]/59.1 mL; PINUS SYLVESTRIS LEAFY TWIG 9 [hp_X]/59.1 mL; SUS SCROFA PITUITARY GLAND 12 [hp_X]/59.1 mL; RANCID BEEF 12 [hp_X]/59.1 mL; SILICON DIOXIDE 12 [hp_X]/59.1 mL; SULFUR 15 [hp_X]/59.1 mL; THUJA OCCIDENTALIS LEAFY TWIG 15 [hp_X]/59.1 mL; THYROID, UNSPECIFIED 9 [hp_X]/59.1 mL; VISCUM ALBUM FRUITING TOP 12 [hp_X]/59.1 mL
INACTIVE INGREDIENTS: WATER 41.361 mL/59.1 mL; ALCOHOL 8.86 mL/59.1 mL; GLYCERIN 8.86 mL/59.1 mL

Lymph-Tone III

ACTIVE INGREDIENT

Adenosinum cyclophosphoricum 12X, 30X; Arnica montana 12X; Boldo 4X, 12X; Calcarea iodata 12X; Calendula officinalis 30X; Cartilago suis 6X, 8X, 12X, 30X; Ceanothus americanus 9X, 12X; Coenzyme A 12X, 30X; DNA 12X, 6C, 30C; Echinacea 4X; Hamamelis virginiana 12X; Hepar sulphuris calcareum 12X; Hypothalamus 12X, 6C; Nadidum 12X, 30X; Naja tripudians 15X; Natrum sulphuricum 30X; Phaseolus 4X, 6X, 12X; Phosphorus 15X, 30X; Phytolacca decandra 4X; Pinus sylvestris 9X; Pituitarum posterium 12X, 6C; Pyrogenium 12X, 30X; Silicea 12X; Sulphur 15X, 30X; Thuja occidentalis 15X; Thyroidinum 9X, 12X, 6C; Viscum album 12X

Do not use if neck wrap imprinted "SEALED FOR YOUR PROTECTION" is broken or missing.

OVERDOSAGE

In case of overdose, get medical help or contact a Poison Control Center right away.

PREGNANCY OR BREAST FEEDING

If pregnant or breast feeding, ask a health professional before use.

Keep out of reach of children.

STORAGE AND HANDLING

Store in cool, dry place out of direct sunlight.

Questions? Comments?

800.990.7085 www.goenergetix.com

PURPOSE

Muscle and joint pain, low vitality, disrupted sleep, disturbed digestion.

INACTIVE INGREDIENT

Purified Water 70%, Glycerin 15%, Ethanol 15%.

DOSAGE AND ADMINISTRATION

Take 30 drops orally twice daily or as directed by a healthcare professional. Shake well before use.

INDICATIONS AND USAGE

Muscle and joint pain, low vitality, disrupted sleep, disturbed digestion.